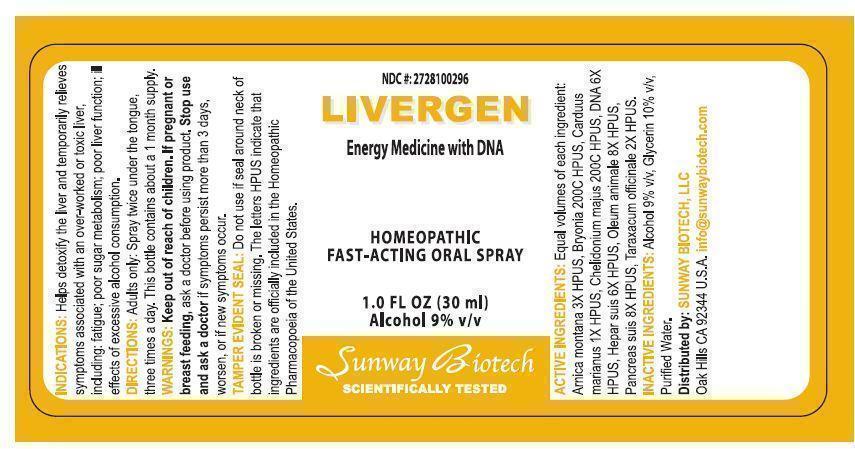 DRUG LABEL: Livergen
NDC: 55138-007 | Form: SPRAY
Manufacturer: Integra Health International, S.A. de C.V.
Category: homeopathic | Type: HUMAN OTC DRUG LABEL
Date: 20131206

ACTIVE INGREDIENTS: ARNICA MONTANA 1.5 [hp_C]/30 mL; BRYONIA ALBA ROOT 200 [hp_C]/30 mL; SILYBUM MARIANUM SEED OIL 0.5 [hp_C]/30 mL; CHELIDONIUM MAJUS 200 [hp_C]/30 mL; HERRING SPERM DNA 3 [hp_C]/30 mL; PORK LIVER 3 [hp_C]/30 mL; CERVUS ELAPHUS HORN OIL 4 [hp_C]/30 mL; SUS SCROFA PANCREAS 4 [hp_C]/30 mL; TARAXACUM OFFICINALE 1 [hp_C]/30 mL
INACTIVE INGREDIENTS: ALCOHOL; GLYCERIN; WATER

ACTIVE INGREDIENT

Active Ingredients: Equal volumes of each ingredient: Arnica Montana 3X HPUS, Bryonia 200C HPUS, Carduus Marianus 1X HPUS, Chelidonium Majus 200C HPUS, DNA 6X HPUS, Hepar Suis 6X HPUS, Oleum Animale 8X HPUS, Pancreas Suis 8X HPUS, Taraxacum Officinale 2X HPUS.

PURPOSE

NDC #: 2728100296

LIVERGEN

Energy Medicine with DNA

Homeopathic Fast-Acting Oral Spray

1.0 Fl Oz (30 ml)

Alcohol 9% v/v

Keep out of reach of children.

INDICATIONS AND USAGE

Indications: Helps detoxify the liver and temporarily relieves symptoms associated with an overworked or toxic liver, including: fatigue; poor sugar metabolism; poor liver function; ill effects of excessive alcohol consumption.

DOSAGE AND ADMINISTRATION

Directions: Adults only: Spray twice under the tongue, three times a day. This bottle contains about a 1 month supply.

WARNINGS

Warnings: Keep out of reach of children. If pregnant or breast feeding, ask a doctor before using product. Stop use and ask a doctor if symptoms persist more than 3 days, worsen, or if new symptoms occur.

OTHER SAFETY INFORMATION

Tamper Evident Seal: Do not use if seal around neck of bottle is broken or missing. The letters HPUS indicate that ingredients are officially included in the Homeopathic Pharmacopoeia of the United States.

INACTIVE INGREDIENT

Inactive Ingredients: Alcohol 8% v/v, Glycerin 10% v/v, Purified Water.